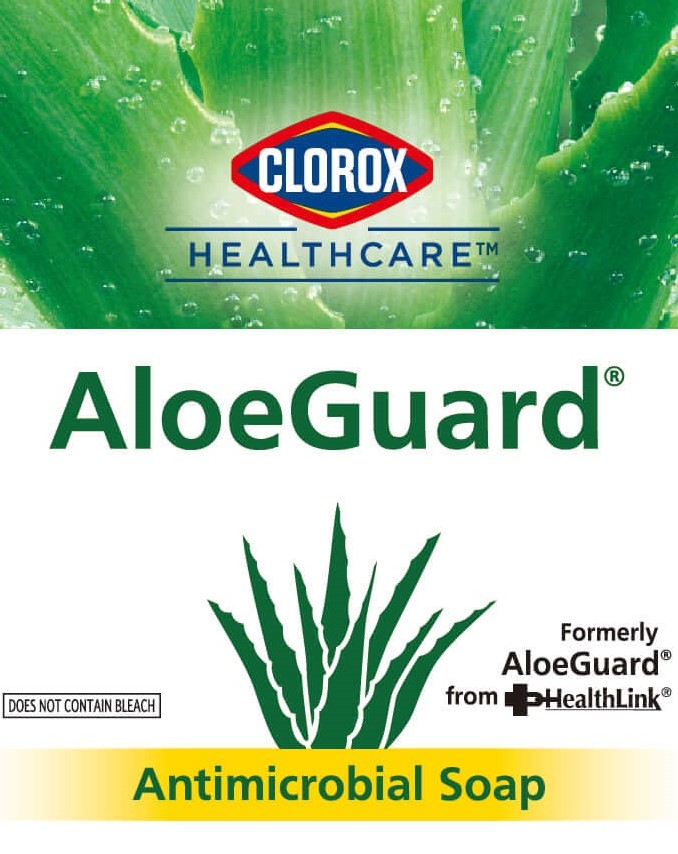 DRUG LABEL: Clorox HealthCare AloeGuard Antimicrobial
NDC: 69540-0027 | Form: LIQUID
Manufacturer: Brand Buzz LLC
Category: otc | Type: HUMAN OTC DRUG LABEL
Date: 20230202

ACTIVE INGREDIENTS: CHLOROXYLENOL 0.75 mg/100 mL
INACTIVE INGREDIENTS: COCO-BETAINE; D&C GREEN NO. 8; OLEIC ACID; PROPYLENE GLYCOL; SODIUM SULFATE; ALOE VERA LEAF; FD&C BLUE NO. 1; FD&C YELLOW NO. 5; GLYCERIN; EDETATE SODIUM; WATER; COCONUT ACID; HYPROMELLOSE, UNSPECIFIED; MONOETHANOLAMINE; COCO MONOETHANOLAMIDE

Clorox HealthCare AloeGuard Antimicrobial Soap

Active ingredient

Chloroxylenol 0.75% w/w

Purpose

Antiseptic

Uses

- for hand-washing to decrease microbes on the skin
- ideal for daily repeated washings

Warnings

For external use only

When using this product

- do not use in or near eyes
- discontue use if irritation and redness develop. If condition persists for more than 72 hours, consult a doctor.

Keep out of reach of children.

In case of accidental ingestion, seek medical attention or contact a poison control center immediately.

Directions

- wet hands
- apply product (palmful)
- wash hands vigorously
- rinse thoroughly

Other information

- store at room temperatuure
- for healthcare professional use only

Inactive ingredients

Aloe Barbadensis Leaf Juice, Cocamide MEA, Coco-Betaine, Coconut Fatty Acid, D&C Green No. 8, FD&C Blue No. 1, FD&C Yellow No. 5, Fragrance, Glycerin, Hydroxypropyl Methylcellulose, Monoethanolamine, Oleic Acid, Propylene Glycol Sodium Sulfate, Tetrasodium EDTA, Water.

Package Label: 118ml/532ml/798ml/3785ml

CLOROX

HEALTHCARE

AloeGuard

Does Not Contain Bleach

Formerly

AloeGuard

from HealthLink

Antimcrobial Soap